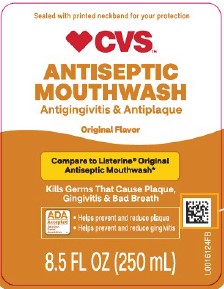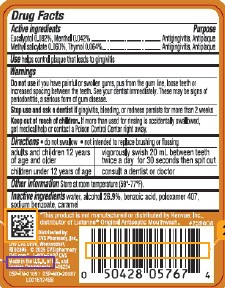 DRUG LABEL: Antiseptic Mouth Rinse
NDC: 59779-898 | Form: MOUTHWASH
Manufacturer: CVS Pharmacy, Inc.
Category: otc | Type: HUMAN OTC DRUG LABEL
Date: 20260203

ACTIVE INGREDIENTS: EUCALYPTOL 0.92 mg/1 mL; MENTHOL 0.42 mg/1 mL; METHYL SALICYLATE 0.6 mg/1 mL; THYMOL 0.64 mg/1 mL
INACTIVE INGREDIENTS: WATER; ALCOHOL; BENZOIC ACID; POLOXAMER 407; SODIUM BENZOATE; CARAMEL

CVS 318.003/318AI
Antiseptic Mouthrinse

Active ingredients

Eucalyptol 0.092%

Menthol 0.042%

Methyl salicylate 0.060%

Thymol 0.064%

Purpose

Antigingivitis, Antiplaque

Use

helps control plaque that leads to gingivitis

Warnings

For this product

Do not use

if you have painful or swollen gums, pus from the gum line, loose teeth or increased spacing between the teeth. See your dentist immediately. These may be signs of periodontitis, a serious form of gum disease.

Stop use and ask a dentist if

gingivitis, bleeding, or redness persists for more than 2 weeks

Keep out of reach of children.

If more than used for rinsing is accidentally swallowed, get medical help or contact a Poison Control Center right away.

Directions

- do not swallow
- not intended to replace brushing or flossing

adults and children 12 years of age and older - vigorously swish 20 mL (2/3 FL OZ or 4 teaspoonfuls) between teeth twice a day for 30 seconds then spit out

children under 12 years of age - consult a dentist or doctor

Other information

Store at room temperature (59°-77°F).

Inactive ingredients

water, alcohol 26.9%, benzoic acid, poloxamer 407, sodium benzoate, caramel

Disclaimer

*This product is manufactued or distributed by Kenvue, Inc., distributor of Listerine® Original Antiseptic Mouthwash.

Adverse reactions

Distributed by: CVS Pharmacy, Inc.

One CVS Drive, Woonsocket, RI 02895

©2025 CVS/pharmacy

CVS.com 1-800-SHOP CVS

Made in the U.S.A. of U.S. and foreign components

DSP-TN-21091

DSP-MO-20087

principal display panel

Sealed with printed neckband for your protection.

CVS™

Antiseptic Mouthwash

Antigingivitis & Antiplaque

Original Flavor

Compare to Listerine® Original Antiseptic Mouthwash*

Kills germs that cause plaque, gingivitis & bad breath

ADA Accepted

American Dental Association

- Helps prevent and reduce plaque
- Helps prevent and reduce gingivitis

8.5 FL OZ (250 mL)